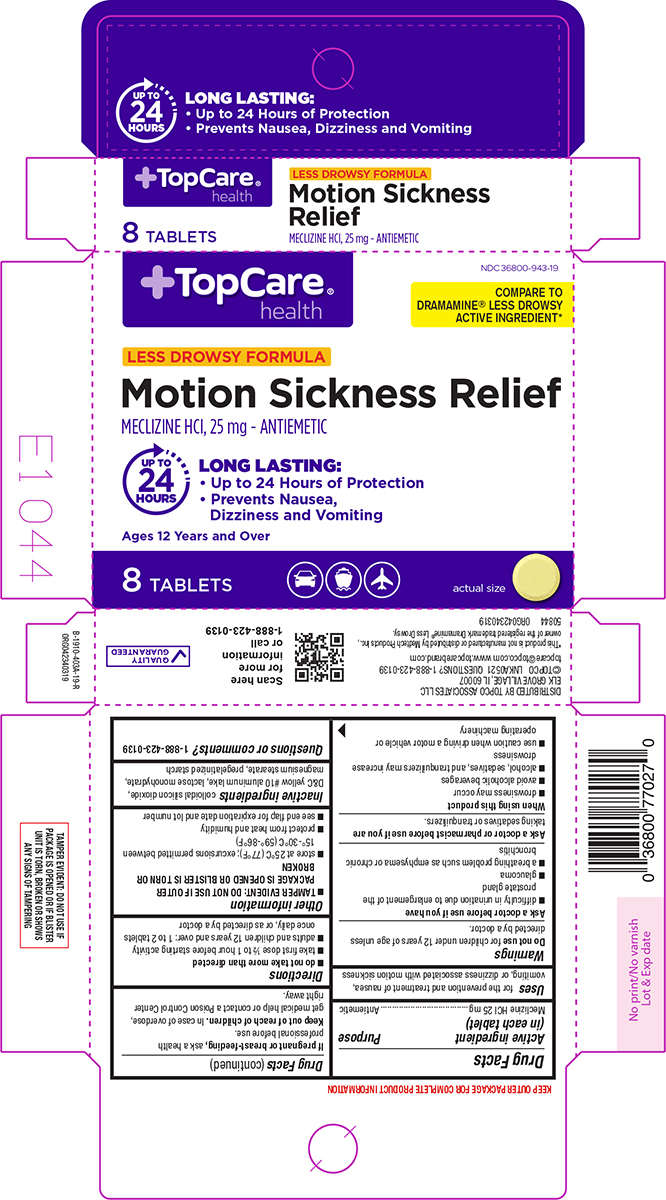 DRUG LABEL: Motion Sickness Relief
NDC: 36800-943 | Form: TABLET
Manufacturer: Topco Associates, LLC
Category: otc | Type: HUMAN OTC DRUG LABEL
Date: 20250719

ACTIVE INGREDIENTS: MECLIZINE HYDROCHLORIDE 25 mg/1 1
INACTIVE INGREDIENTS: SILICON DIOXIDE; D&C YELLOW NO. 10 ALUMINUM LAKE; LACTOSE MONOHYDRATE; MAGNESIUM STEARATE; STARCH, CORN

Topcare 44-403A

Active ingredient (in each tablet)

Meclizine HCl 25 mg

Purpose

Antiemetic

Uses

for the prevention and treatment of nausea, vomiting, or dizziness associated with motion sickness

Warnings

Do not use

for children under 12 years of age unless directed by a doctor.

Ask a doctor before use if you have

- difficulty in urination due to enlargement of the prostate gland
- glaucoma
- a breathing problem such as emphysema or chronic bronchitis

Ask a doctor or pharmacist before use if you are

taking sedatives or tranquilizers.

When using this product

- drowsiness may occur
- avoid alcoholic beverages
- alcohol, sedatives, and tranquilizers may increase drowsiness
- use caution when driving a motor vehicle or operating machinery

If pregnant or breast-feeding,

ask a health professional before use.

Keep out of reach of children.

In case of overdose, get medical help or contact a Poison Control Center right away.

Directions

- do not take more than directed
- take first dose ½ to 1 hour before starting activity
- adults and children 12 years and over: 1 to 2 tablets once daily, or as directed by a doctor

Other information

- TAMPER EVIDENT: DO NOT USE IF OUTER PACKAGE IS OPENED OR BLISTER IS TORN OR BROKEN
- store at 25°C (77°F); excursions permitted between 15°-30°C (59°-86°F)
- protect from heat and humidity
- see end flap for expiration date and lot number

Inactive ingredients

colloidal silicon dioxide, D&C yellow #10 aluminum lake, lactose monohydrate, magnesium stearate, pregelatinized starch

Questions or comments?

1-888-423-0139

Principal display panel

+TopCare®
health

NDC 36800-943-19

COMPARE TO
DRAMAMINE® LESS DROWSY
ACTIVE INGREDIENT*

LESS DROWSY FORMULA

Motion Sickness Relief
MECLIZINE HCl, 25 mg - ANTIEMETIC

LONG LASTING:
• Up to 24 Hours of Protection
• Prevents Nausea,
Dizziness and Vomiting

Ages 12 Years and Over

UP TO
24
HOURS

8 TABLETS

actual size

TAMPER EVIDENT: DO NOT USE IF
PACKAGE IS OPENED OR IF BLISTER
UNIT IS TORN, BROKEN OR SHOWS
ANY SIGNS OF TAMPERING

DISTRIBUTED BY TOPCO ASSOCIATES LLC
ELK GROVE VILLAGE, IL 60007
©TOPCO LNKA0521 QUESTIONS? 1-888-423-0139
topcare@topco.com www.topcarebrand.com

*This product is not manufactured or distributed by Medtech Products Inc.,
owner of the registered trademark Dramamine® Less Drowsy.

50844 ORG042340319

QUALITY
GUARANTEED

TopCare 44-403